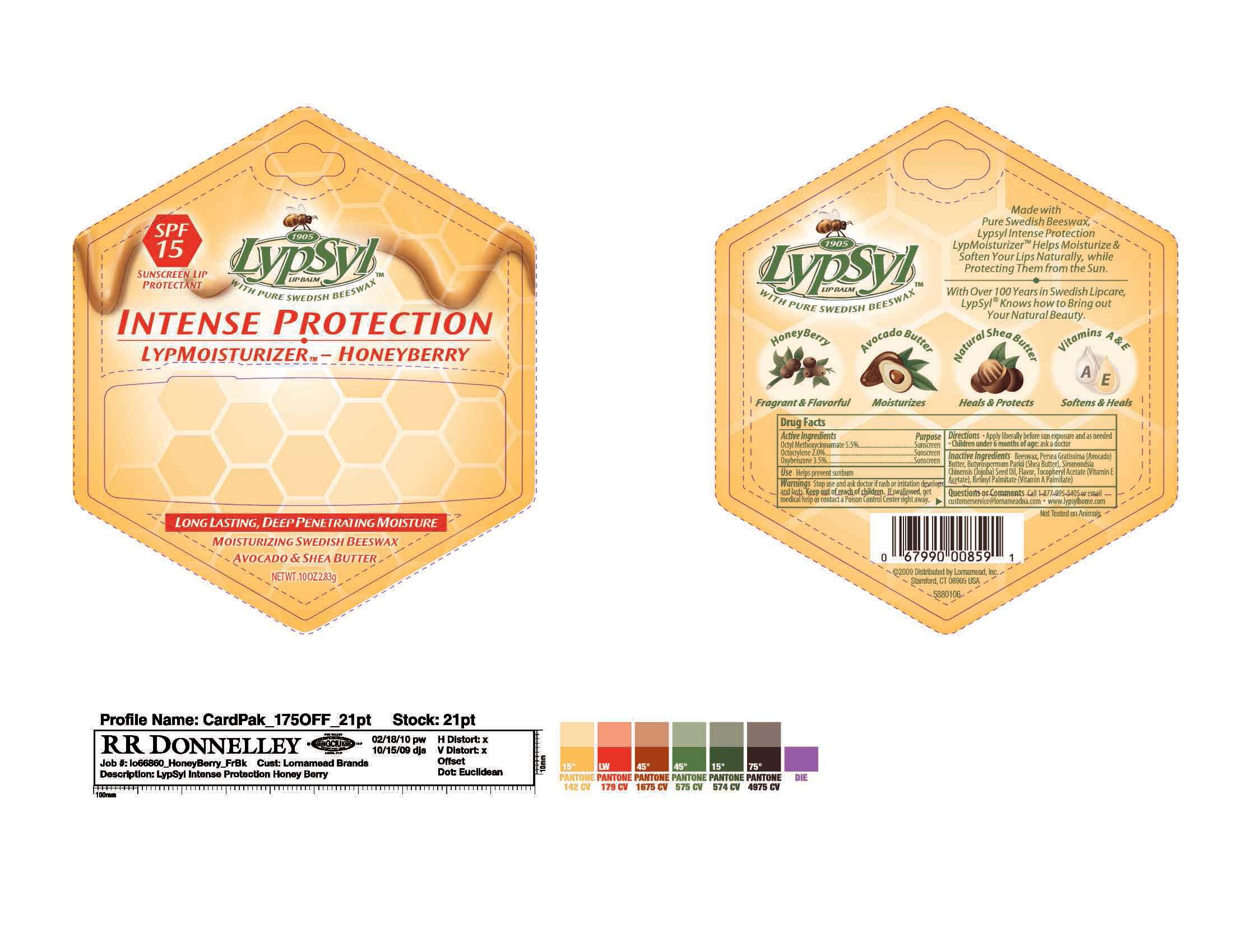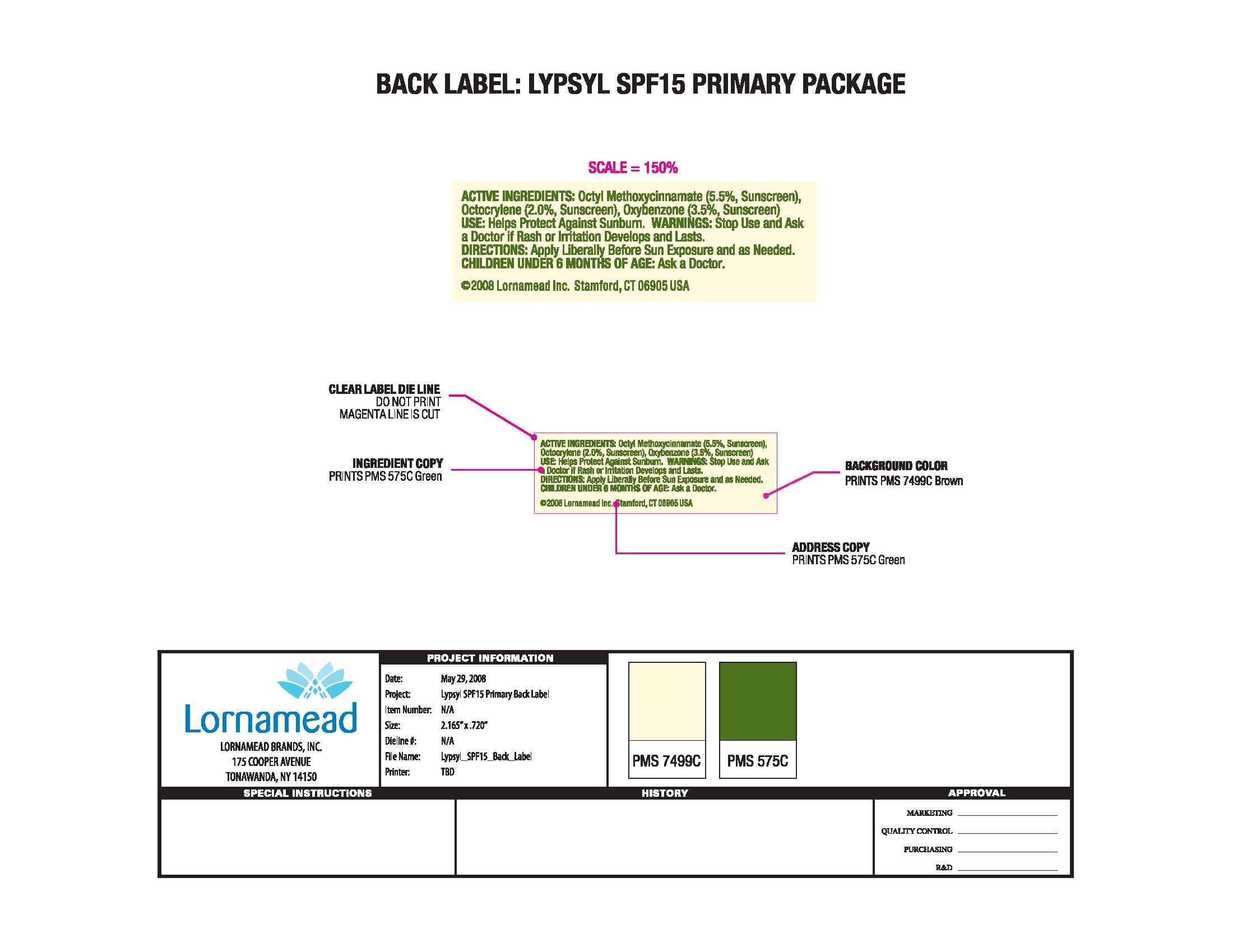 DRUG LABEL: LypSyl Honeyberry
NDC: 62721-8106 | Form: LIPSTICK
Manufacturer: Lornamead
Category: otc | Type: HUMAN OTC DRUG LABEL
Date: 20181227

ACTIVE INGREDIENTS: OCTINOXATE 5.5 g/100 g; OCTOCRYLENE 2 g/100 g; OXYBENZONE 3.5 g/100 g
INACTIVE INGREDIENTS: VITAMIN A PALMITATE 0.1 g/100 g; ALPHA-TOCOPHEROL 0.5 g/100 g; YELLOW WAX 24 g/100 g; JOJOBA OIL 19.4 g/100 g; PERSEA AMERICANA SEED BUTTER 22.3 g/100 g; SHEA BUTTER 21 g/100 g

Drug Facts

Active ingredients

Octyl Methoxycinnamate 5.5%
Octocrylene 2.0%
Oxybenzone 3.5%

Use

Sunscreen

Stop use and ask a doctor -

if rash or irritation develops and lasts

Keep out of reach of children. If swallowed, get medical help or contact a Poison Control

Center right away.

Directions

Apply liberally before sun exposure and as needed

children under 6 months of age:

ask a doctor

Questions or Comments

Call 1-877-995-5405 or email customerservice@lornameadna.com - www.lypsylhome.com

Inactive ingredients

Beeswax, Persea Gratissima (Avocado), Butter, Butyrospermum Parkii (Shea Butter), Simmondsia,
Chinensis (Jojoba) Seed Oil, Flavor, Tocopheryl Acetate (Vitamin E Acetate), Retinyl Palmitate (Vitamin A Palmitate)

DOSAGE AND ADMINISTRATION

Apply liberally before sun exposure and as needed